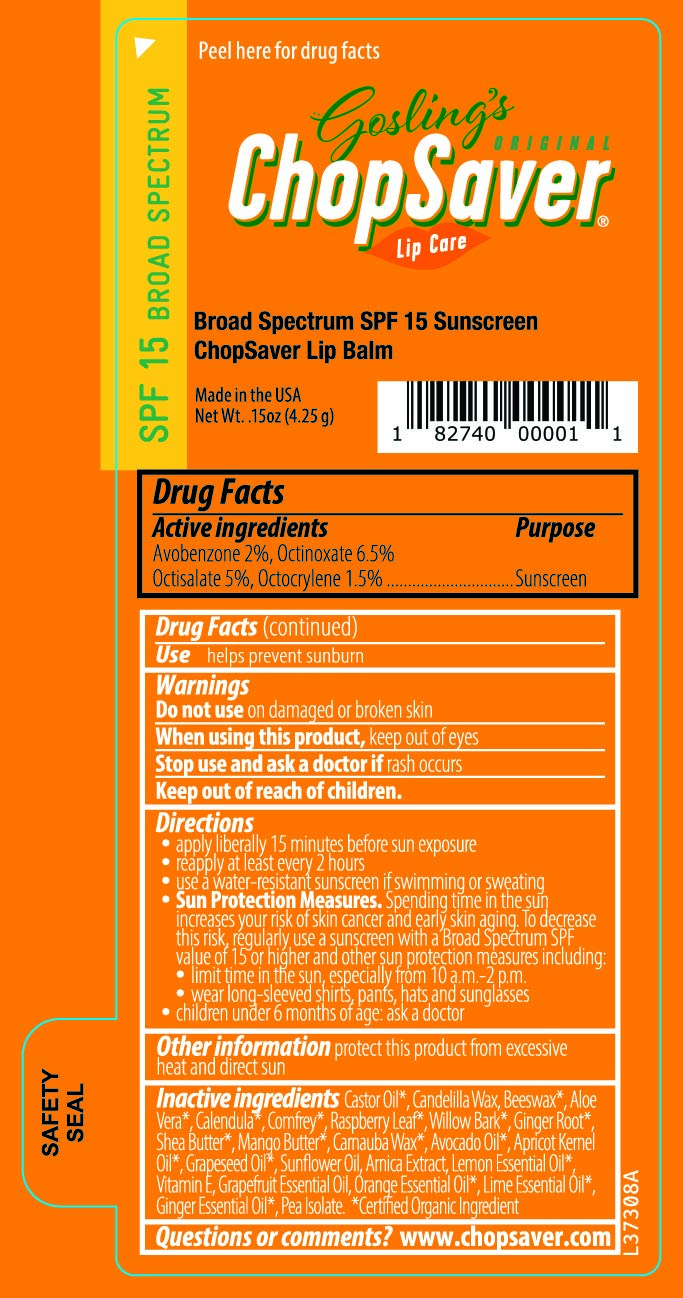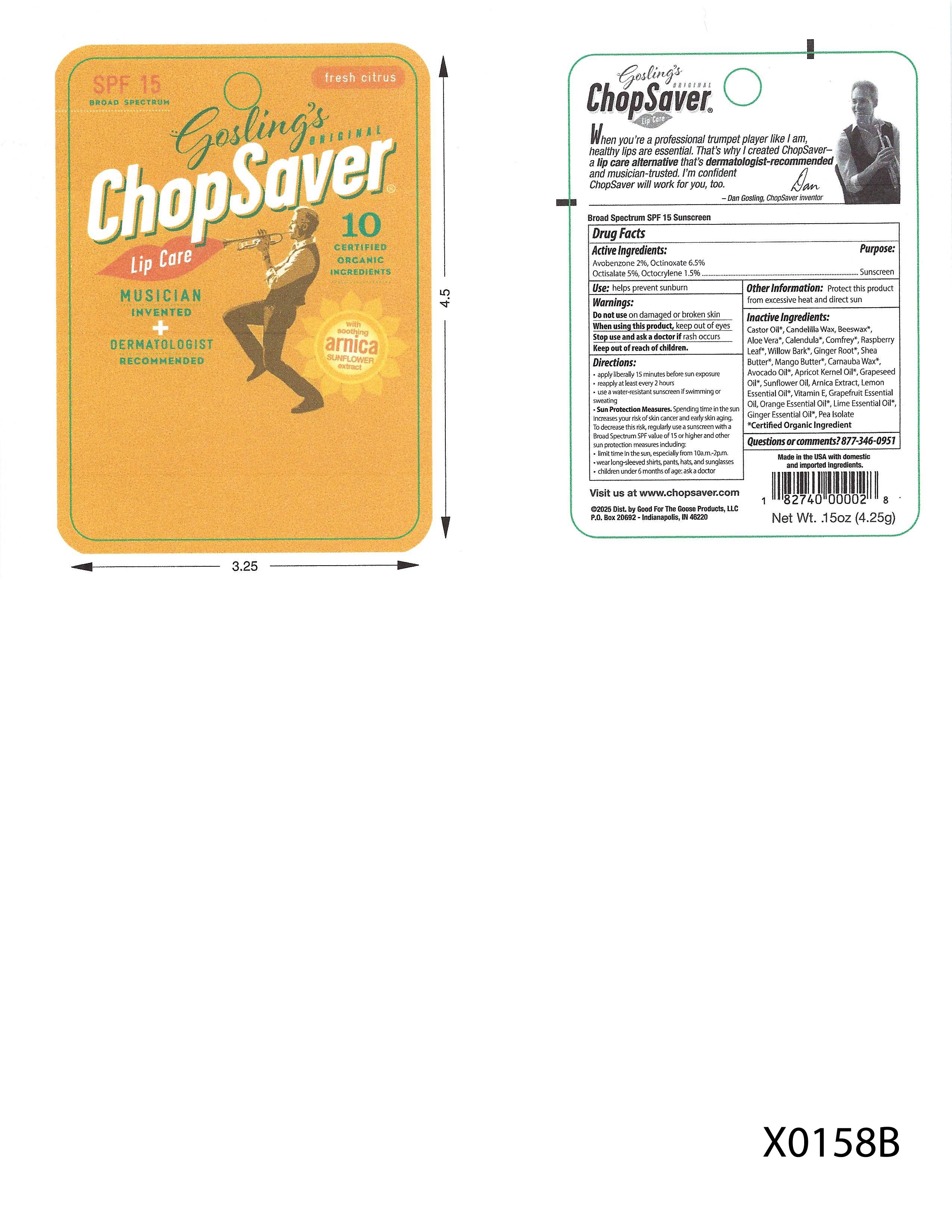 DRUG LABEL: AVOBENZONE,OCTINOXATE,OCTISALATE,OCTOCRYLENE
NDC: 83724-770 | Form: STICK
Manufacturer: Good for the Goose Products, LLC
Category: otc | Type: HUMAN OTC DRUG LABEL
Date: 20251023

ACTIVE INGREDIENTS: AVOBENZONE 2 g/100 g; OCTINOXATE 6.5 g/100 g; OCTISALATE 5 g/100 g; OCTOCRYLENE 1.5 g/100 g
INACTIVE INGREDIENTS: CASTOR OIL; CANDELILLA WAX; YELLOW WAX; SHEA BUTTER; MANGIFERA INDICA SEED BUTTER; CARNAUBA WAX; AVOCADO OIL; APRICOT KERNEL OIL; GRAPE SEED OIL; LEMON OIL, DISTILLED; .ALPHA.-TOCOPHEROL; GRAPEFRUIT OIL; ORANGE OIL, DISTILLED; LIME OIL, DISTILLED; GINGER OIL; ARNICA MONTANA WHOLE; CALENDULA OFFICINALIS FLOWER; RUBUS IDAEUS LEAF; COMFREY LEAF; ALOE VERA LEAF; SALIX ALBA WHOLE; PEA PROTEIN

92770 Chop Saver Fresh Citrus SPF 15 Lip Balm

Drug Facts

Active Ingredients:

Avobenzone 2%, Octinoxate 6.5%

Octisalate 5%, Octocrylene 1.5%

Purpose:

Sunscreen

INDICATIONS AND USAGE

Use: Helps prevent sunburn

Warnings:

Do not use on damaged or broken skin

When using this product, keep out of eyes

Stop use and ask a doctor if rash occurs

Keep out of reach of children.

Directions:

- apply liberally 15 minutes before sun exposure
- reapply at least every 2 hours
- use a water-resistant sunscreen if swimming or sweating
- Sun protection measures. Spending time in the

sun increases your risk of skin cancer and early

skin aging. To decrease this risk, regularly use a

sunscreen with Broad Spectrum SPF value of 15 or

higher and other sun protection measures including:

- limit time in the sun, especially from 10am-2pm.
- wear long-sleeved shirts, pants, hats and sunglasses
- children under 6 months of age: ask a doctor

Other information:Protect this product

from excessive heat and direct sun

Inactive Ingredients:

Castor Oil*, Candelilla Wax, Beeswax*,

Aloe Vera*, Calendula*, Comfrey*, Raspberry

Leaf*, Willow Bark*, Ginger Root*, Shea

Butter*, Mango Butter*, Carnauba Wax*,

Avocado Oil*, Arnica Extract, Lemon

Essential Oil*, Vitamin E, Grapefruit Essential

Oil, Orange Essential Oil*, Lime Essential Oil*,

Ginger Essential Oil*, Pea Isolate

*Certified Organic Ingredient

Questions or comments? 877-346-0951

Blister Card Content

SPF 15 Broad Spectrum

Fresh Citrus

Gosling's Original

ChopSaver

Lip Care

10 Certified Organic Ingredients

Musician Invented

Dermatologist Recommended

with soothing arnica sunflower extract

When you're a proefessional trumpet player like I am,

healthy lips are essential. That's why I created ChopSaver-

a lip care alternative that's dermatologist-recommended

and musician-trusted. I'm confident

ChopSaver will work for you , too.

-Dan Gosling,ChopSaver Inventor

Broad Spectrum SPF 15 Sunscreen

Visit us at www.chopsaver.com

(c) 2019 Good For the Goose Products, LLC

P.O. Box 20692 - Indianapolis, IN 46220

Made in the USA with domestic

and imported ingredients

Net Wt. .15 oz (4.25 g)

Tube Label Content

Peel here for Drug Facts

SPF 15 Broad Spectrum

Gosling's Original

ChopSaver Lip Care

Broad Spectrum SPF 15 Sunscreen

ChopSaver Lip Balm

Made in the USA

Net Wt. .15 oz (4.25 g)

RECENT MAJOR CHANGES

Dosage and Administration section updated to read:

Directions:

- apply liberally 15 minutes before sun exposure
- reapply at least every 2 hours
- use a water-resistant sunscreen if swimming or sweating
- Sun protection measures. Spending time in the

sun increases your risk of skin cancer and early

skin aging. To decrease this risk, regularly use a

sunscreen with Broad Spectrum SPF value of 15 or

higher and other sun protection measures including:

- limit time in the sun, especially from 10am-2pm.
- wear long-sleeved shirts, pants, hats and sunglasses
- children under 6 months of age: ask a doctor